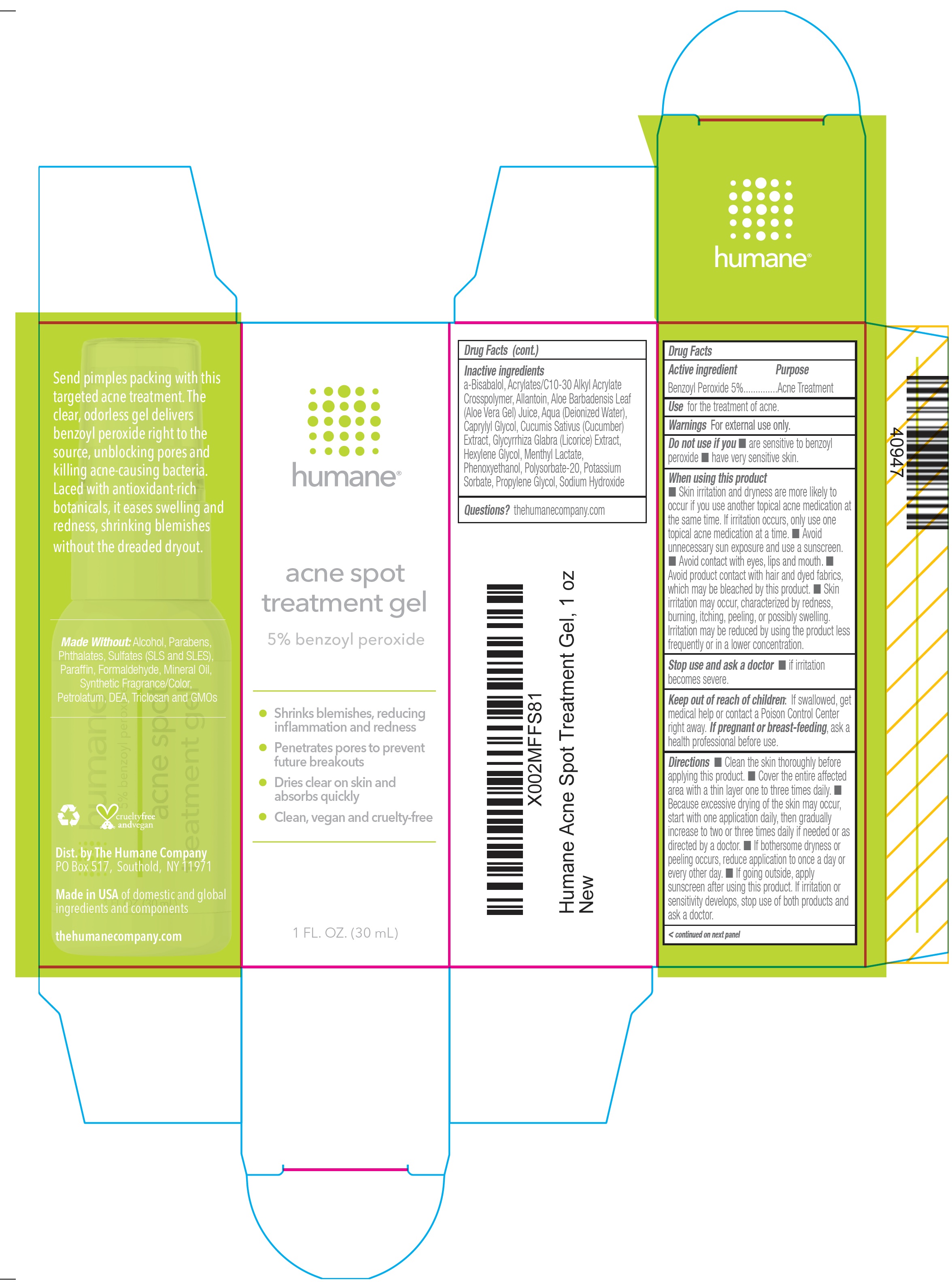 DRUG LABEL: HUMANE Acne Spot Treatment
NDC: 73010-127 | Form: GEL
Manufacturer: Apprendista, LLC
Category: otc | Type: HUMAN OTC DRUG LABEL
Date: 20231111

ACTIVE INGREDIENTS: BENZOYL PEROXIDE 50 mg/1 mL
INACTIVE INGREDIENTS: CARBOMER INTERPOLYMER TYPE A (ALLYL SUCROSE CROSSLINKED); ALLANTOIN; ALOE VERA LEAF; WATER; CAPRYLYL GLYCOL; CUCUMBER; LICORICE; HEXYLENE GLYCOL; MENTHYL LACTATE, (-)-; PHENOXYETHANOL; POLYSORBATE 20; POTASSIUM SORBATE; PROPYLENE GLYCOL; SODIUM HYDROXIDE

HUMANE Acne Spot Treatment Gel

Active ingredient

Benzoyl Peroxide 5%

Purpose

Acne Treatment

Use

for the treatment of acne.

Warnings

For external use only.

Do not use if you

- are sensitive to benzoyl peroxide
- have very sensitive skin.

When using this product

- Skin irritation and dryness are more likely to occur if you use another topical acne medication at the same time. If irritation occurs, only use one topical acne medication at a time.
- Avoid unnecessary sun exposure and use a sunscreen.
- Avoid contact with eyes, lips and mouth. Avoid product contact with hair and dyed fabrics, which may be bleached by this product.
- Skin irritation may occur, characterized by redness, burning, itching, peeling, or possibly swelling. Irritation may be reduced by using the product less frequently or in a lower concentration.

Stop use and ask a doctor

if irritation becomes severe.

Keep out of reach of children:

If swallowed, get medical help or contact a Poison Control Center right away.

If pregnant or breast-feeding,

ask a health professional before use.

Directions

- Clean the skin thoroughly before applying this product.
- Cover the entire affected area with a thin layer one to three times daily.
- Because excessive drying of the skin may occur, start with one application daily, then gradually increase to two or three times daily if needed or as directed by a doctor.
- If bothersome dryness or peeling occurs, reduce application to once a day or every other day.
- If going outside, apply sunscreen after using this product. If irritation or sensitivity develops, stop use of both products and ask a doctor.

Inactive ingredients

a-Bisabalol, Acrylates/C10-30 Alkyl Acrylate Crosspolymer, Allantoin, Aloe Barbadensis Leaf (Aloe Vera Gel) Juice, Aqua (Deionized Water), Caprylyl Glycol, Cucumis Sativus (Cucumber) Extract, Glycyrrhiza Glabra (Licorice) Extract, Hexylene Glycol, Menthyl Lactate, Phenoxyethanol, Polysorbate-20, Potassium Sorbate, Propylene Glycol, Sodium Hydroxide

Questions?

thehumanecompany.com